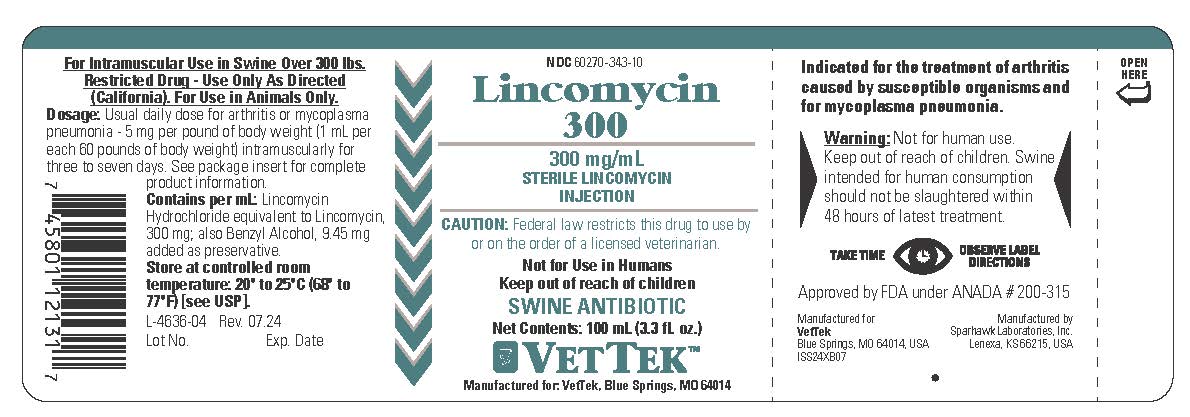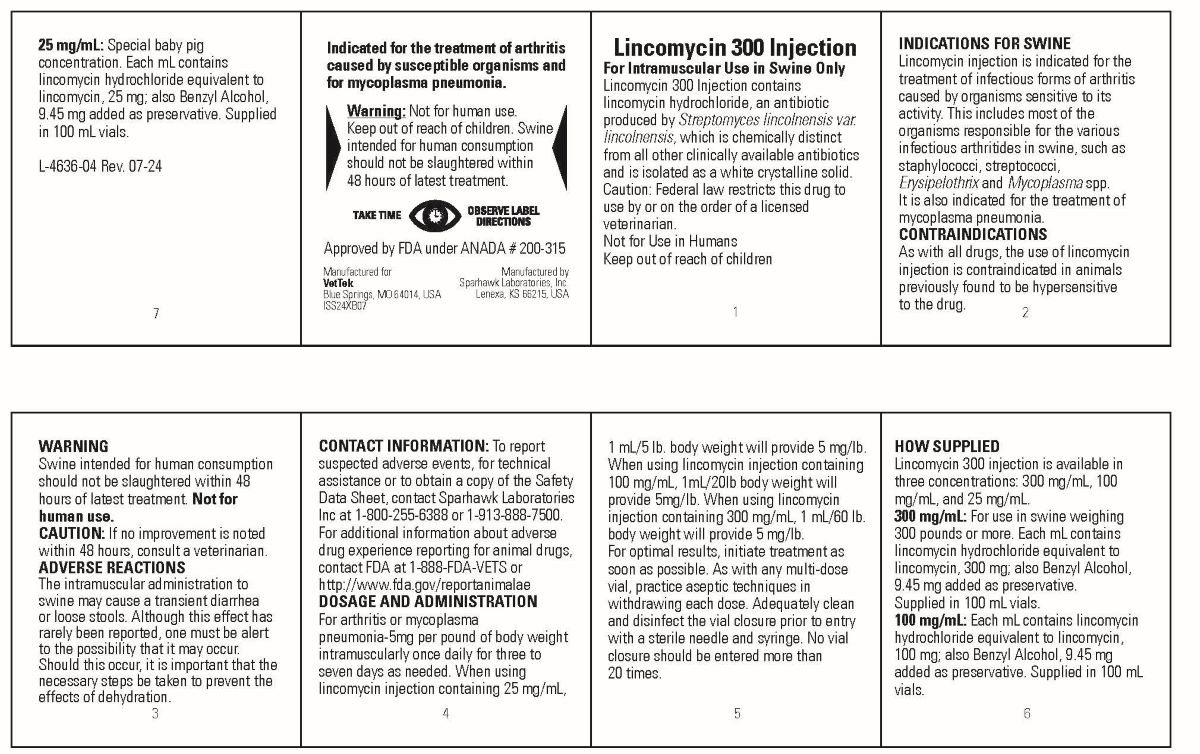 DRUG LABEL: LINCOMYCIN 
NDC: 60270-343 | Form: INJECTION
Manufacturer: VetTek
Category: animal | Type: PRESCRIPTION ANIMAL DRUG LABEL
Date: 20250701

ACTIVE INGREDIENTS: LINCOMYCIN HYDROCHLORIDE 300 mg/1 mL

LINCOMYCIN 300 INJECTION

INDICATIONS AND USAGE

300 mg/mL

STERILE LINCOMYCIN INJECTION

Caution:Federal law restricts this drug to use by or on the order of a licenced veterinarian.

Not for Use in Humans
Keep out of reach of children

SWINE ANTIBIOTIC

For Intramuscular Use in Swine Over 300 lbs.
Restricted Drug - Use Only As Directed
(California). For Use in Animals Only

Indicated for the treatment of arthritis caused by susceptible organisims and for mycoplasma pneumonia.

Lincomycin Injectable contains lincomycin hydrochloride, an antibiotic produced bySteptomyces lincolnensis var. lincolnensis, which is chemically distinct from all other clinically avaialbel antibiotics and is isolated as a white crystalline solid

Caution: Federal law restricts this drug to use by or on the order of a licensed veterinarian.
Not for Use in Humans
Keep out of reach of children

INDICATIONS FOR SWINE

Lincomycin injectable is indicated for the treatment of infectious forms of arthritis caused by organisms sensitive to its activity. This includes most of the organisms responsible for the various infectious arthritides in swine, such as staphylococci, streptococci,Erysipelothrix and Mycoplasma spp.

CONTRAINDICATIONS

As with all drugs, the use of Lincomycin Injectable is contraindicated in animals previously found to be hypersensitive to the drug.

WARNING

Swine intended for human consumption should not be slaughtered within 48 hours of latest treatment. Not for human use.

CAUTION

If no improvement is noted within 48 hours, consult a veterinarian.

ADVERSE REACTIONS

The intramuscular administration to swine may cause a transient diarrhea or loose stools. Although this effect had rarely been reported, one must be alert to the possibility that it may occur. Should this occur, it is important that the necessary steps be taken to prevent the effects of dehydration.

CONTACT INFORMATION

To report suspected adverse events, for technical assistance or to obtain a copy of the Safety Data Sheet, contact Sparhawk Laboratories Inc at 1-800-255-6388 or 1-913-888-7500. For additional information about adverse drug experience reporting for animal drugs, contact FDA at 1-888-FDA-VETS or http://www.fda.gov/reportanimalae

DOSAGE AND ADMINISTRATION

For arthritis or mycoplasma pneumonia-5mg per pound of body weight intramuscularly once daily for three to seven days as needed. When using lincomycin injection containing 25 mg/mL, 1 mL/5 lb. body weight will provide 5 mg/lb.
When using lincomycin injection containing 100 mg/mL, 1mL/20lb body weight will provide 5mg/lb. When using lincomycin injection containing 300 mg/mL, 1 mL/60 lb. body weight will provide 5 mg/lb.
For optimal results, initiate treatment as soon as possible. As with any multi-dose vial, practice aseptic techniques in withdrawing each dose. Adequately clean and disinfect the vial closure prior to entry with a sterile needle and syringe. No vial closure should be entered more than 20 times.

HOW SUPPLIED

Lincomycin Injectable is available in three concentrations: 300 mg/mL, 100 mg/mL and 25 mg/mL

300 mg/mL: For use in swine weighing 300 pounds or more. Each mL contains lincomycin hydrochloride equivalent to lincomycin, 300 mg, also Benzyl Alcohol, 9.45 mg added as preservative. Supplied in 100 mL vials.

100 mg/mL: Each mL contains lincomycin hydrochloride equivalent to lincomycin, 100 mg; also Benzyl Alcohol, 9,45 mg added as preservative. Supplied in 100 mL vials.

25 mg/mL: Special baby pig concentration. Each mL contains lincomycin hydrochloride equivalent to lincomycin, 25 mg; also Benyl Alcohol, 9.45 mg added as preservative. Supplied in 100 mL vials.

STORAGE AND HANDLING

Store at controlled room temperature: 20o to 25oC (68o to 77oF) [see USP]